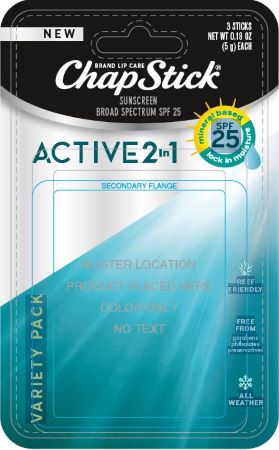 DRUG LABEL: Chapstick Active 2in1

NDC: 0573-0803 | Form: KIT | Route: TOPICAL
Manufacturer: Haleon US Holdings LLC
Category: otc | Type: HUMAN OTC DRUG LABEL
Date: 20240411

ACTIVE INGREDIENTS: ZINC OXIDE 500 mg/1 g; ZINC OXIDE 500 mg/1 g; ZINC OXIDE 500 mg/1 g
INACTIVE INGREDIENTS: ALOE VERA LEAF; ARGAN OIL; ASTROCARYUM MURUMURU SEED BUTTER; YELLOW WAX; SHEA BUTTER; MEDIUM-CHAIN TRIGLYCERIDES; SAFFLOWER OIL; COCONUT OIL; CARNAUBA WAX; CANDELILLA WAX; SUNFLOWER OIL; HYDROGENATED JOJOBA OIL/JOJOBA OIL, RANDOMIZED (IODINE VALUE 57-61); HYDROGENATED JOJOBA OIL, RANDOMIZED; MANGIFERA INDICA SEED BUTTER; POLYHYDROXYSTEARIC ACID (2300 MW); TOCOPHEROL; .ALPHA.-TOCOPHEROL ACETATE; ALOE VERA LEAF; ARGAN OIL; ASTROCARYUM MURUMURU SEED BUTTER; YELLOW WAX; .ALPHA.-BISABOLOL, (+/-)-; SHEA BUTTER; MEDIUM-CHAIN TRIGLYCERIDES; SAFFLOWER OIL; COCONUT OIL; CARNAUBA WAX; CANDELILLA WAX; SUNFLOWER OIL; HYDROGENATED JOJOBA OIL, RANDOMIZED; MANGIFERA INDICA SEED; POLYHYDROXYSTEARIC ACID (2300 MW); TOCOPHEROL; .ALPHA.-TOCOPHEROL ACETATE; ALOE VERA LEAF; ARGAN OIL; ASTROCARYUM MURUMURU SEED BUTTER; YELLOW WAX; .ALPHA.-BISABOLOL, (+/-)-; SHEA BUTTER; MEDIUM-CHAIN TRIGLYCERIDES; SAFFLOWER; COCONUT OIL; CARNAUBA WAX; CANDELILLA WAX; SUNFLOWER OIL; HYDROGENATED JOJOBA OIL, RANDOMIZED; MANGIFERA INDICA SEED BUTTER; POLYHYDROXYSTEARIC ACID (2300 MW); CASTOR OIL; TOCOPHEROL; .ALPHA.-TOCOPHEROL ACETATE

Drug Facts

Active ingredient

Zinc Oxide 20.5%

Purpose

Sunscreen

Uses

- helps prevent sunburn
- if used as directed with other sun protection measures (see Directions), decreases the risk of skin cancer and early skin aging caused by the sun

Warnings

For external use only

Do not use

- on damaged or broken skin

When using this product

- keep out of eyes. Rinse with water to remove.

Keep out of reach of children.

If swallowed, get medical help or contact a Poison Control Center right away.

Directions

- apply liberally 15 minutes before sun exposure
- reapply at least every 2 hours
- use a water resistant sunscreen if swimming or sweating
- children under 6 months of age:

Ask a doctor

Sun Protection Measures. Spending time in the sun increases your risk of skin cancer and early skin aging. To decrease this risk, regularly use a sunscreen with a Broad Spectrum SPF value of 15 or higher and other sun protection measures including:

- limit time in the sun, especially from 10 a.m. – 2 p.m.
- wear long-sleeved shirts, pants, hats and sunglasses

Other information

- store at 20-25°C (68-77°F)
- protect the product from excessive heat and direct sun

Inactive ingredients (Unscented)

aloe barbadensis leaf extract, argania spinosa kernel oil, astrocaryum murumuru seed butter, beeswax,

bisabolol, butyrospermum parkii (shea) butter, caprylic/capric triglyceride, carthamus tinctorius

(safflower) seed oil, cocos nucifera (coconut) oil, copernicia cerifera (carnauba) wax, euphorbia

cerifera (candelilla) wax, helianthus annuus (sunflower) seed oil, jojoba esters, mangifera indica

(mango) seed butter, polyhydroxystearic acid, tocopherol, tocopheryl acetate

Inactive ingredients (Fresh Mint)

aloe barbadensis leaf extract, argania spinosa kernel oil, astrocaryum murumuru seed butter, beeswax,

bisabolol, butyrospermum parkii (shea) butter, caprylic/capric triglyceride, carthamus tinctorius (safflower) seed oil, cocos nucifera (coconut) oil, copernicia cerifera (carnauba) wax, euphorbia cerifera

(candelilla) wax, helianthus annuus (sunflower) seed oil, jojoba esters, mangifera indica (mango) seed

butter, natural flavors, polyhydroxystearic acid, tocopherol, tocopheryl acetate, yellow 6 lake

Inactive ingredients (Wild Berry)

aloe barbadensis leaf extract, argania spinosa kernel oil, astrocaryum murumuru seed butter, beeswax,

bisabolol, butyrospermum parkii (shea) butter, caprylic/capric triglyceride, carthamus tinctorius

(safflower) seed oil, cocos nucifera (coconut) oil, copernicia cerifera (carnauba) wax, euphorbia

cerifera (candelilla) wax, helianthus annuus (sunflower) seed oil, jojoba esters, mangifera indica

(mango) seed butter, natural flavors, polyhydroxystearic acid, ricinus communis (castor) seed oil,

tocopherol, tocopheryl acetate

Questions or comments?

call weekdays from 8 AM to 6 PM at 1-800-245-1040

Additional information

Paraben Free

Dist. by: GSK CH, Warren, NJ 07059

For most recent product information, visit www.chapstick.com

Trademarks owned or licensed by GSK

©2022 GSK or licensor

For US Patent or Application status see www.productpats.com

200219

Principal Display Panel

ChapStick®

NEW

BRAND LIP CARE

SUNSCREEN

BROAD SPECTRUM SPF 25

ACTIVE 2in1

mineral based SPF 25lock in moisture

VARIETY PACK

REEF FRIENDLY

FREE FROM

parabens

phthalates

preservatives

ALL WEATHER

3 STICKS
NET WT 0.18 OZ
(5 g) EACH

200219